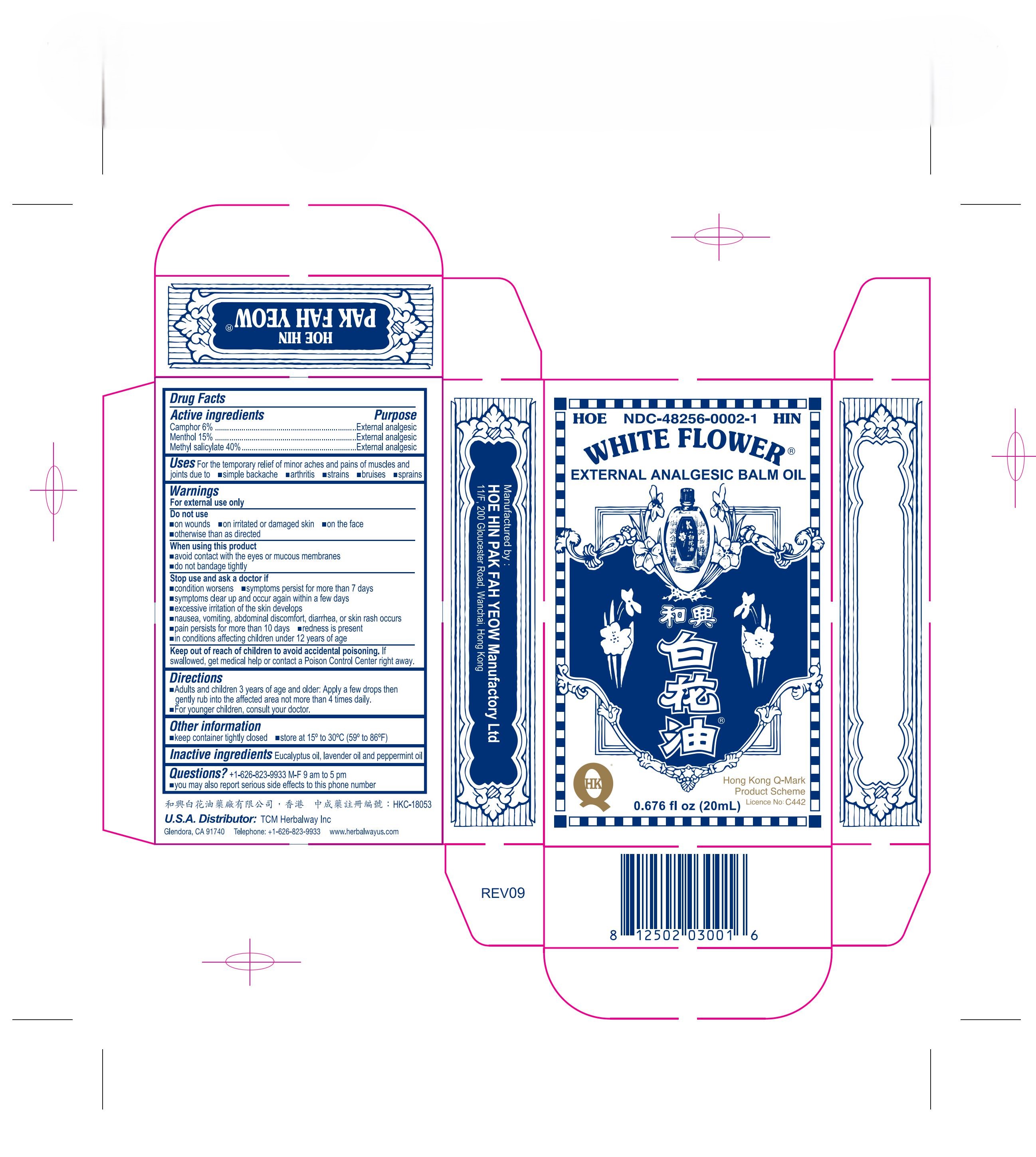 DRUG LABEL: WHITE FLOWER ANALGESIC BALM
NDC: 48256-0002 | Form: OIL
Manufacturer: HOE HIN PAK FAH YEOW MANUFACTORY LTD
Category: otc | Type: HUMAN OTC DRUG LABEL
Date: 20251021

ACTIVE INGREDIENTS: CAMPHOR (SYNTHETIC) 6 g/100 mL; MENTHOL 14.5 g/100 mL; METHYL SALICYLATE 40.02 g/100 mL
INACTIVE INGREDIENTS: EUCALYPTUS OIL; LAVENDER OIL; PEPPERMINT OIL

DRUG FACTS

Active ingredients

Camphor 6%

Menthol 15%

Methyl salicylate 40%

Purpose

External analgesic

Do not use

- on wounds
- on irritated or damaged skin
- on the face
- otherwise than as directed

When using this product

- avoid contact with the eyes or mucous membranes
- do not bandage tightly

Stop use and ask a doctor if

- condition worsens
- symptoms persist for more than 7 days
- symptoms clear up and occur again within a few days
- excessive irritation of the skin develops
- nausea, vomiting, abdominal discomfort, diarrhea, or skin rash occurs
- pain persists for more than 10 days
- redness is present
  - in conditions affecting children under 12 years of age

Keep out of reach of children to avoid accidental poisoning

If swallowed, get medical help or contact a Poison Control Center right away.

Directions

- Adults and children 3 years of age and older: Apply a few drops then gently rub into the affected area not more than 4 times daily.
- For younger children, consult your doctor.

Other information

- keep container tightly closed
- store at 15º to 30ºC (59º to 86ºF)

Inactive ingredients

Eucalyptus oil, lavender oil and peppermint oil.

QUESTIONS

Questions? +1-626-823-9933 M-F 9am to 5pm

- you may also report serious side effects to this phone number

INDICATIONS AND USAGE

Uses For the temporary relief of minor aches and pains of muscles and joints due to

- simple backache
- arthritis
- strains
- bruises
- sprains

Warnings

For external use only

PACKAGE LABEL

White Flower Analgesic Balm NDC-48256-0002 0.676 fl oz (20mL)